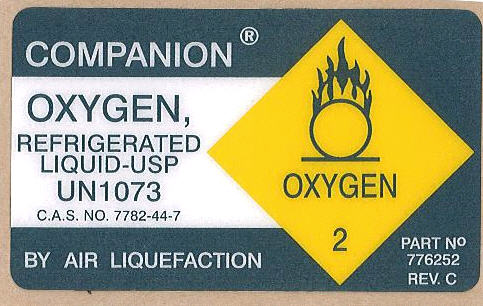 DRUG LABEL: Liquid Oxygen 
NDC: 60317-123 | Form: GAS
Manufacturer: Pedi Stat Inc.
Category: prescription | Type: HUMAN PRESCRIPTION DRUG LABEL
Date: 20100810

ACTIVE INGREDIENTS: Oxygen 995 mL/1 L

Liquid Oxygen

PRINCIPAL DISPLAY PANEL

COMPANION®
OXYGEN,
REFRIGERATED
LIQUID-USP
UN1073
C.A.S. NO. 7782-44-7
BY AIR LIQUEFACTION
PART No
776252
REV. C